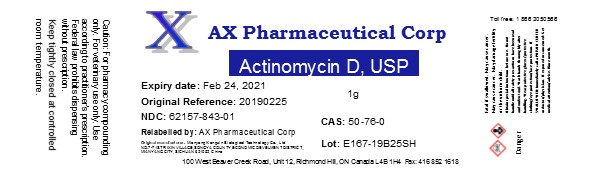 DRUG LABEL: Actinomycin D
NDC: 62157-843 | Form: POWDER
Manufacturer: AX Pharmaceutical Corp
Category: other | Type: BULK INGREDIENT
Date: 20190516

ACTIVE INGREDIENTS: DACTINOMYCIN 1 g/1 g

Actinomycin D